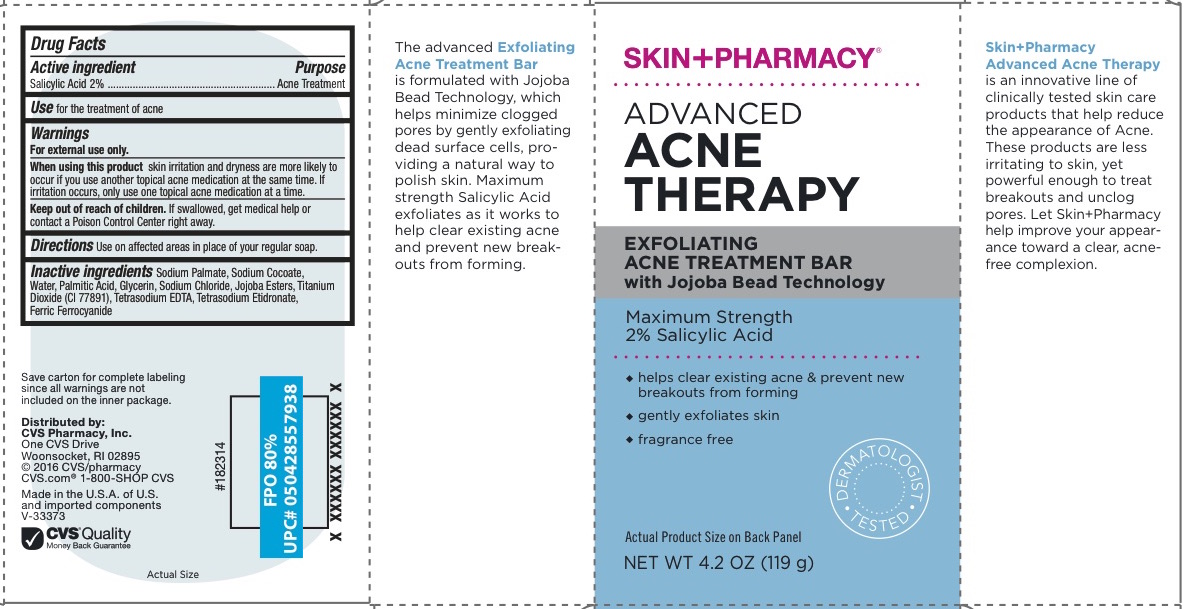 DRUG LABEL: ADVANCED ACNE THERAPY
NDC: 69842-342 | Form: SOAP
Manufacturer: CVS Pharmacy, Inc.
Category: otc | Type: HUMAN OTC DRUG LABEL
Date: 20160614

ACTIVE INGREDIENTS: SALICYLIC ACID 2 g/100 g
INACTIVE INGREDIENTS: WATER; SODIUM PALMATE; SODIUM COCOATE; PALMITIC ACID; GLYCERIN; SODIUM CHLORIDE; ETIDRONATE TETRASODIUM; EDETATE SODIUM; HYDROGENATED JOJOBA OIL; TITANIUM DIOXIDE; FERRIC FERROCYANIDE

ADVANCED ACNE THERAPY

Active Ingredient

Salicylic Acid 2%

Purpose

Acne Treatment

Use

For for the treatment of acne

Warnings

For external use only

- Keep out of the reach of children.
- If swallowed, get medical help or contact a Poison Control Center immediately.

Directions

- Use on affected areas in place of your regular soap

When using this product skin irritation and dryness are more likely to occur if you use another topical acne medication at the same time. If irritation occurs, only use one topical acne medication at a time.

INACTIVE INGREDIENT

Sodium Palmate, Sodium Cocoate, Water, Palmitic Acid, Glycerin, Sodium Chloride, Jojoba Esters, Titanium Dioxide (CI 77891), Tetrasodium EDTA, Tetrasodium Etidronate, Ferric Ferrocyanide

Questions?

www.CVS.com

1-800-SHOP CVS